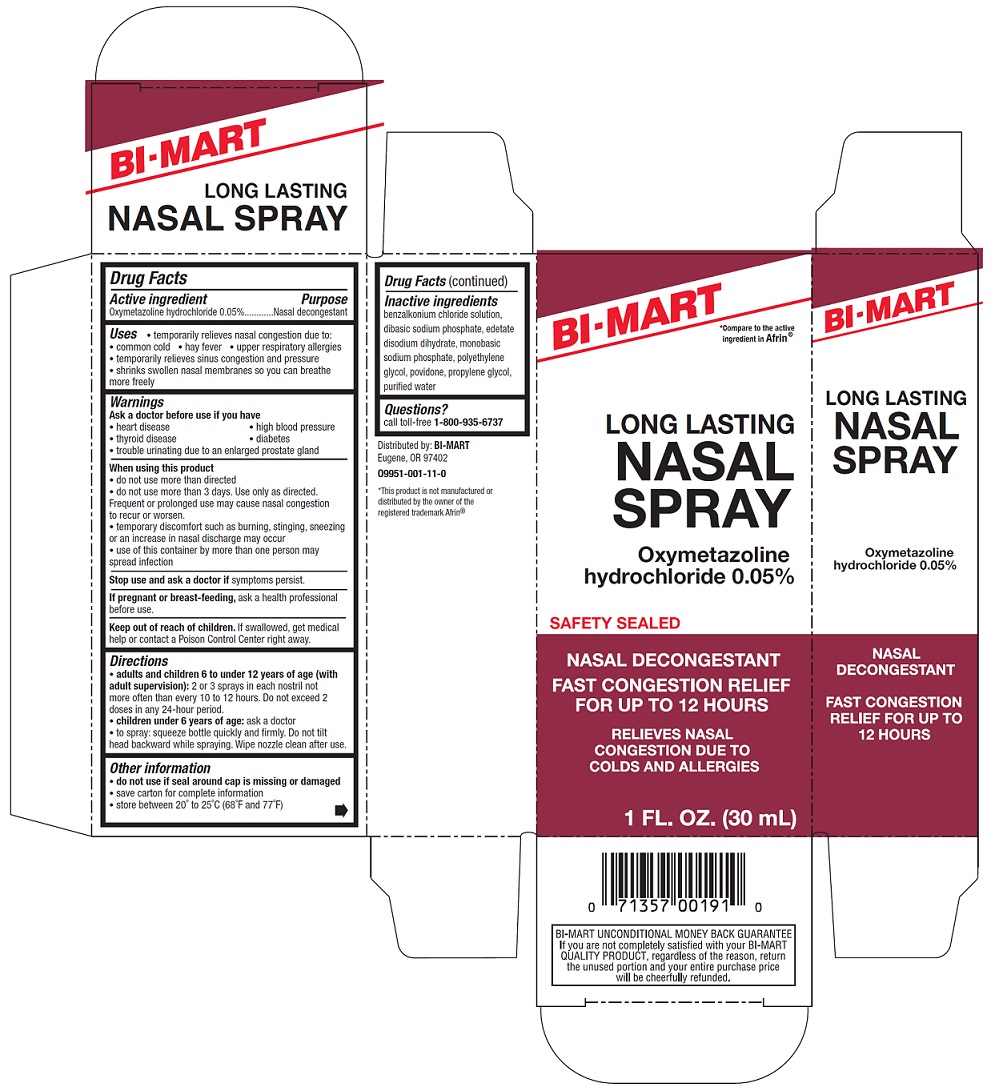 DRUG LABEL: NASAL
NDC: 37835-995 | Form: SPRAY
Manufacturer: Bi-Mart
Category: otc | Type: HUMAN OTC DRUG LABEL
Date: 20240516

ACTIVE INGREDIENTS: OXYMETAZOLINE HYDROCHLORIDE 0.05 g/100 mL
INACTIVE INGREDIENTS: BENZALKONIUM CHLORIDE; SODIUM PHOSPHATE, DIBASIC, UNSPECIFIED FORM; EDETATE DISODIUM; SODIUM PHOSPHATE, MONOBASIC, UNSPECIFIED FORM; POLYETHYLENE GLYCOL, UNSPECIFIED; POVIDONE; PROPYLENE GLYCOL; WATER

NASAL SPRAY

Drug Facts

Active ingredient

Oxymetazoline hydrochloride 0.05%

Purpose

Nasal decongestant

Uses

- temporarily relieves nasal congestion due to:
  - common cold
  - hay fever
  - upper respiratory allergies
- temporarily relieves sinus congestion and pressure
- shrinks swollen nasal membranes so you can breathe more freely

Warnings

Ask a doctor before use if you have

- heart disease
- high blood pressure
- thyroid disease
- diabetes
- trouble urinating due to an enlarged prostate gland

When using this product

- do not use more than directed
- do not use for more than 3 days. Use only as directed. Frequent or prolonged use may cause nasal congestion to recur or worsen.
- temporary discomfort such as burning, stinging, sneezing or an increase in nasal discharge may occur
- use of this container by more than one person may spread infection

Stop use and ask a doctor ifsymptoms persist.

PREGNANCY OR BREAST FEEDING

If pregnant or breast-feeding, ask a health professional before use.

Keep out of reach of children.If swallowed, get medical help or contact a Poison Control Center right away.

Directions

- adults and children 6 to under 12 years of age (with adult supervision):2 or 3 sprays in each nostril not more often than every 10 to 12 hours. Do not exceed 2 doses in any 24-hour period.
- children under 6 years of age:ask a doctor.
- to spray: squeeze bottle quickly and firmly. Do not tilt head backward while spraying. Wipe nozzle clean after use.

Other information

- do not use if seal around cap is missing or damaged
- save carton for complete information
- store between 20° to 25°C (68°F and 77°F)

Inactive ingredients

benzalkonium chloride solution, dibasic sodium phosphate, edetate disodium dihydrate, monobasic sodium phosphate, polyethylene glycol, povidone, propylene glycol, purified water.

Questions?

call toll-free 1-800-935-6737

Distributed by:

BI-MART

Eugene, OR 97402

*This product is not manufactured or distributed by the owner of the registered trademark Afrin®

PRINCIPAL DISPLAY PANEL

BI-MART

*Compare to the active ingredient in Afrin®

LONG LASTING

NASAL SPRAY

Oxymetazoline hydrochloride 0.05%

NASAL DECONGESTANT

FAST CONGESTION RELIEF FOR UP TO 12 HOURS

RELIEVES NASAL CONGESTION DUE TO COLDS AND ALLERGIES

1 FL. OZ. (30 mL)